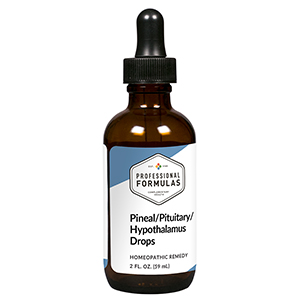 DRUG LABEL: Pineal/Pituitary/Hypothalamus Drops
NDC: 63083-5022 | Form: LIQUID
Manufacturer: Professional Complementary Health Formulas
Category: homeopathic | Type: HUMAN OTC DRUG LABEL
Date: 20190815

ACTIVE INGREDIENTS: CHASTE TREE FRUIT 3 [hp_X]/59 mL; BOS TAURUS HYPOTHALAMUS 6 [hp_X]/59 mL; SUS SCROFA PINEAL GLAND 6 [hp_X]/59 mL; BOS TAURUS PITUITARY GLAND, POSTERIOR 6 [hp_X]/59 mL; STRYCHNOS IGNATII SEED 12 [hp_X]/59 mL; PHOSPHORIC ACID 12 [hp_X]/59 mL; PICRIC ACID 12 [hp_X]/59 mL
INACTIVE INGREDIENTS: ALCOHOL; WATER

HPPH

ACTIVE INGREDIENTS

Agnus castus 3X
Hypothalamus 6X, 12X, 30X, 60X, 100X
Pineal 6X, 12X, 30X, 60X, 100X
Pituitary 6X, 12X, 30X, 60X, 100X
Ignatia amara 12X
Phosphoricum acidum 12X
Picricum acidum 12X

QUESTIONS

Professional Formulas

PO Box 2034 Lake Oswego, OR 97035

INDICATIONS

For the temporary relief of fatigue, weakness, sadness, sleep disturbance, minor muscle aches, occasional headache, dizziness, mood changes or swings, dry skin, weight gain, or constipation.*

PURPOSE

*Claims based on traditional homeopathic practice, not accepted medical evidence. Not FDA evaluated.

WARNINGS

In case of overdose, get medical help or contact a poison control center right away.

Keep out of the reach of children.

PREGNANCY OR BREAST FEEDING

If pregnant or breastfeeding, ask a healthcare professional before use.

DIRECTIONS

Place drops under tongue 30 minutes before/after meals. Adults and children 12 years and over: Take 10 drops up to 3 times per day. Consult a physician for use in children under 12 years of age.

OTHER INFORMATION

Tamper resistant. If seal is broken, do not use. After opening, close container tightly and store at room temperature away from heat.

INACTIVE INGREDIENTS

20% ethanol, purified water.

LABEL

Est 1985

Professional Formulas

Complementary Health

Pineal/Pituitary/Hypothalamus Drops

Homeopathic Remedy

2 FL. OZ. (59 mL)